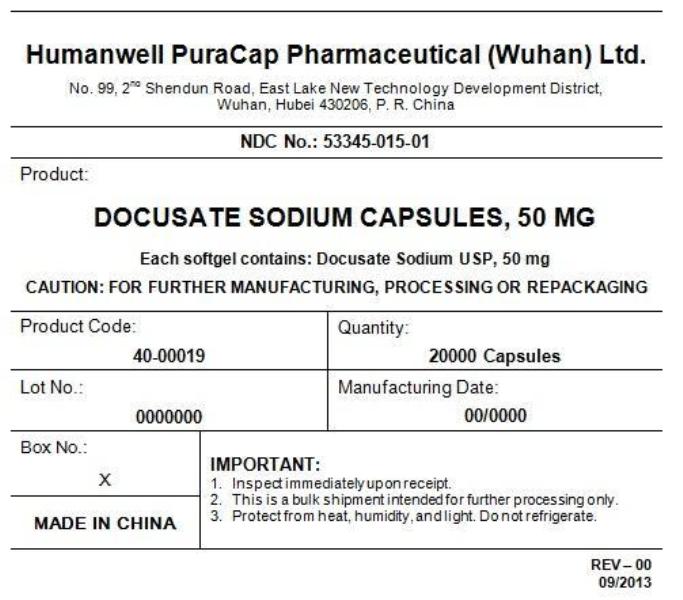 DRUG LABEL: DOCUSATE SODIUM 50 MG
NDC: 53345-015 | Form: CAPSULE, LIQUID FILLED
Manufacturer: Humanwell PuraCap Pharmaceutical (Wuhan), Ltd.
Category: otc | Type: HUMAN OTC DRUG LABEL
Date: 20241125

ACTIVE INGREDIENTS: DOCUSATE SODIUM 50 mg/1 1
INACTIVE INGREDIENTS: FD&C RED NO. 40; D&C RED NO. 33; FD&C YELLOW NO. 6; GELATIN; GLYCERIN; POLYETHYLENE GLYCOL, UNSPECIFIED; PROPYLENE GLYCOL; WATER; SORBITOL; ANHYDROUS CITRIC ACID

DOCUSATE SODIUM 50mg, Capsule, liquid filled

Drug Facts

Active ingredient (in each softgel)

Docusate Sodium 50 mg

Purpose

Stool softener

Uses

- relieves occasional constipation (irregularity)
- generally produces bowel movement in 12 to 72 hours

Warnings

Do not use

- if you are presently taking mineral oil, unless told to do so by a doctor

Ask a doctor before use if you have

- stomach pain
- nausea
- vomiting
- noticed a sudden change in bowel habits that lasts over 2 weeks

Stop use and ask a doctor if

- you have rectal bleeding or fail to have a bowel movement after use of a laxative. These could be signs of a serious condition.
- you need to use a stool softener laxative for more than 1 week

PREGNANCY OR BREAST FEEDING

If pregnant or breast-feeding,ask a health professional before use.

Keep out of reach of children.In case of overdose, get medical help or contact a Poison Control Center right away.

Directions

Take only by mouth. Doses may be taken as a single daily dose or in divided doses.

Adults and children 12 years of ages and over | take 1 to 6 softgels daily
Children 2 and under 12 years of age | take 1 to 3 softgels daily
children under 2 years of age | ask a doctor

Other information

- each softgel contains: sodium 3 mg VERY LOW SODIUM
- store at 15°-30°C (59°-86°F)
  Keep tightly closed.

Inactive ingredients

citric acid, D&C red #33, FD&C red #40, FD&C yellow #6, gelatin, glycerin, polyethylene glycol, propylene glycol, purified water, sorbitol special, white edible ink

Manufactured by:
Humanwell PuraCap Pharmaceutical (Wuhan) Ltd.
Wuhan, Hubei
430206, China

PRINCIPAL DISPLAY PANEL - Shipping Label

DOCUSATE SODIUM CAPSULES, 50 mg

Quantity : 20000 Capsules
NDC. No : 53345-015-01

IMPORTANT:

Inspect immediate upon receipt.
This is a bulk shipment intended for further processing only.
Protect from heat, humidity, and light. Do not refrigerate.

CAUTION : "FOR FURTHER MANUFACTURING, PROCESSING OR REPACKING"